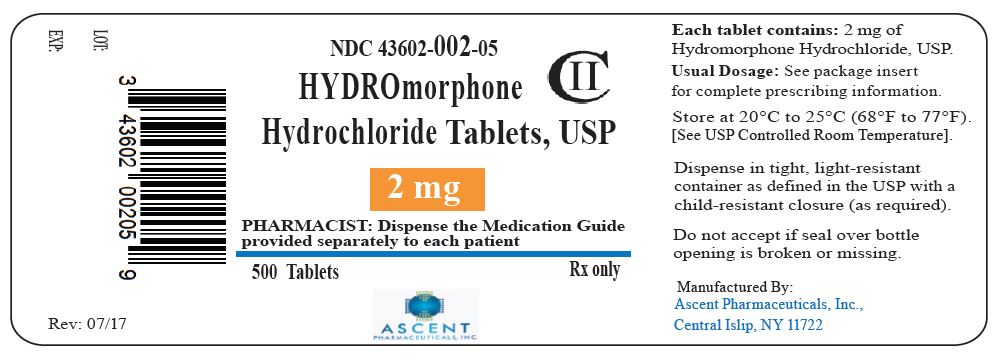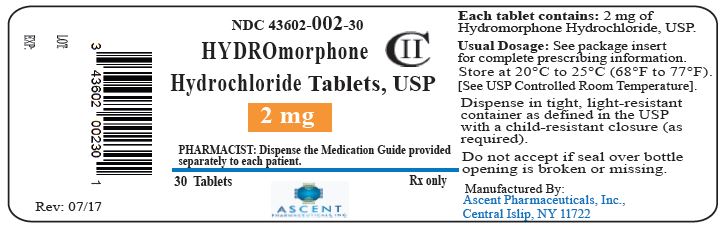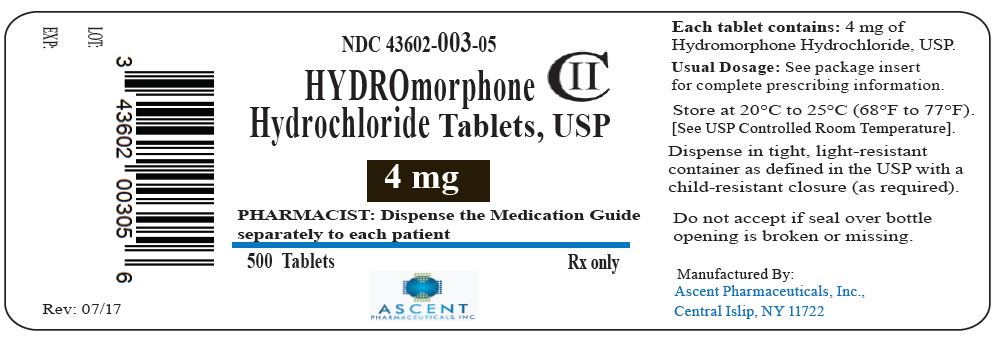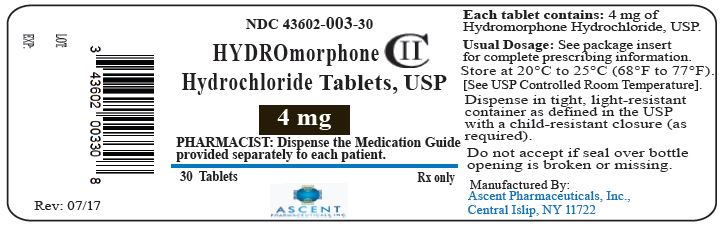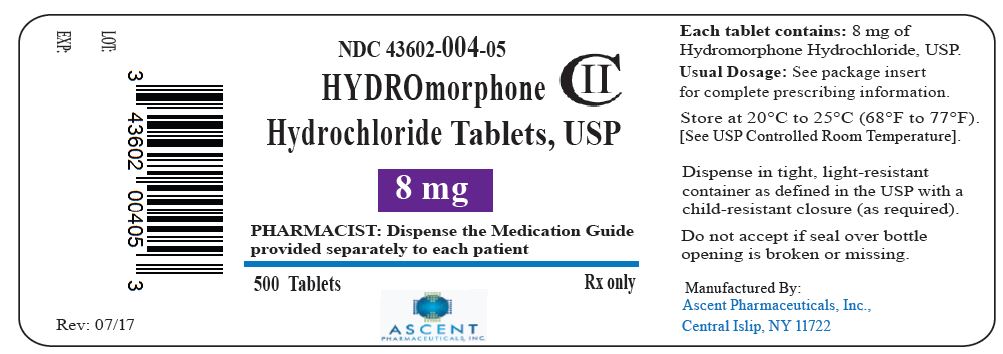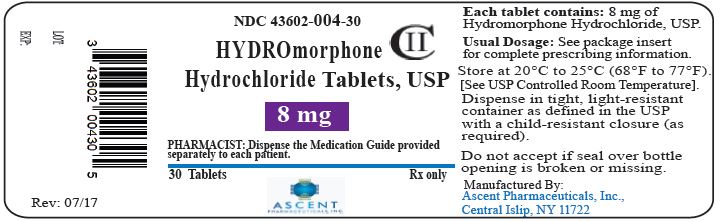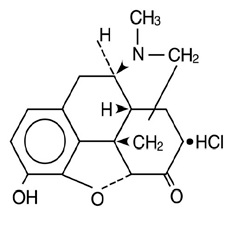 DRUG LABEL: HYDROMORPHONE HYDROCHLORIDE
NDC: 43602-002 | Form: TABLET
Manufacturer: Ascent Pharmaceuticals Inc
Category: prescription | Type: HUMAN PRESCRIPTION DRUG LABEL
Date: 20240904
DEA Schedule: CII

ACTIVE INGREDIENTS: HYDROMORPHONE HYDROCHLORIDE 2 mg/1 1
INACTIVE INGREDIENTS: ANHYDROUS LACTOSE; CELLULOSE, MICROCRYSTALLINE; MAGNESIUM STEARATE; SODIUM METABISULFITE; D&C RED NO. 30; D&C YELLOW NO. 10

HIGHLIGHTS OF PRESCRIBING INFORMATION

These highlights do not include all the information needed to use HYDROMORPHONE HYDROCHLORIDE TABLETS safely and effectively. See full prescribing information for HYDROMORPHONE HYDROCHLORIDE TABLETS.
HYDROMORPHONE HYDROCHLORIDE tablets, for oral use, C-II
Initial U.S. Approval: January 1984

WARNING: RISK OF MEDICATION ERRORS; ADDICTION, ABUSE, AND MISUSE; LIFE-THREATENING RESPIRATORY DEPRESSION; ACCIDENTAL INGESTION; NEONATAL OPIOID WITHDRAWAL SYNDROME; and RISKS FROM CONCOMITANT USE WITH BENZODIAZEPINES OR OTHER CNS DEPRESSANTS

WARNING: RISK OF MEDICATION ERRORS; ADDICTION, ABUSE, AND MISUSE; LIFE-THREATENING RESPIRATORY DEPRESSION; ACCIDENTAL INGESTION; NEONATAL OPIOID WITHDRAWAL SYNDROME; RISKS FROM CONCOMITANT USE WITH BENZODIAZEPINES OR OTHER CNS DEPRESSANTS

See full prescribing information for complete boxed warning.

- Hydromorphone Hydrochloride Tablets exposes users to risks of addiction, abuse, and misuse, which can lead to overdose and death. Assess patient’s risk before prescribing and monitor regularly for these behaviors and conditions. (5.2)
- Serious, life-threatening, or fatal respiratory depression may occur. Monitor closely, especially upon initiation or following a dose increase. (5.3)
- Accidental ingestion of Hydromorphone Hydrochloride Tablets, especially by children, can result in a fatal overdose of hydromorphone. (5.3)
- Prolonged use of Hydromorphone Hydrochloride Tablets during pregnancy can result in neonatal opioid withdrawal syndrome, which may be life-threatening if not recognized and treated. If prolonged opioid use is required in a pregnant woman, advise the patient of the risk of neonatal opioid withdrawal syndrome and ensure that appropriate treatment will be available. (5.4)
- Concomitant use of opioids with benzodiazepines or other central nervous system (CNS) depressants, including alcohol, may result in profound sedation, respiratory depression, coma, and death. Reserve concomitant prescribing for use in patients for whom alternative treatment options are inadequate; limit dosages and durations to the minimum required; and follow patients for signs and symptoms of respiratory depression and sedation. (5.5, 7).

RECENT MAJOR CHANGES

Boxed Warning | 12/2016
Indications and Usage (1) | 12/2016
Dosage and Administration (2) | 12/2016
Warnings and Precautions (5) | 12/2016

1 INDICATIONS AND USAGE

Hydromorphone Hydrochloride Tablets contain hydromorphone, an opioid agonist, and are indicated for the management of pain severe enough to require an opioid analgesic and for which alternative treatments are inadequate.

Limitations of Use

Because of the risks of addiction, abuse, and misuse with opioids, even at recommended doses, reserve Hydromorphone Hydrochloride Tablets for use in patients for whom alternative treatment options [e.g., non-opioid analgesics or opioid combination products]:

- Have not been tolerated, or are not expected to be tolerated,
- Have not provided adequate analgesia, or are not expected to provide adequate analgesia

2 DOSAGE AND ADMINISTRATION

- Use the lowest effective dosage for the shortest duration consistent with individual patient treatment goals.
- Individualize dosing based on the severity of pain, patient response, prior analgesic experience, and risk factors for addiction, abuse, and misuse. (2.1)
- Usual adult starting dose for Hydromorphone Hydrochloride Tablets is 2 mg to 4 mg, orally, every 4 to 6 hours. (2.2)
- Hepatic Impairment: Initiate treatment with one-fourth to one-half the usual starting dose, depending on degree of hepatic impairment. (2.3)
- Renal Impairment: Initiate treatment with one-fourth to one-half the usual starting dose, depending on degree of renal impairment. (2.4)
- Do not stop Hydromorphone Hydrochloride Tablets abruptly in a physically-dependent patient. (2.5)

3 DOSAGE FORMS AND STRENGTHS

- Hydromorphone Hydrochloride Tablets, USP: 2 mg, 4 mg, 8 mg (3)

4 CONTRAINDICATIONS

- Significant respiratory depression. (4)
- Acute or severe bronchial asthma in an unmonitored setting or in absence of resuscitative equipment. (4)
- Known or suspected gastrointestinal obstruction, including paralytic ileus. (4)
- Known hypersensitivity to hydromorphone, hydromorphone salts, or sulfite- containing medications (4)

5 WARNINGS AND PRECAUTIONS

- Life-Threatening Respiratory Depression in Patients with Chronic Pulmonary Diseaseor in Elderly, Cachectic, or Debilitated Patients: Monitor closely, particularly during initiation and titration. (5.6)
- Adrenal Insufficiency:If diagnosed, treat with physiologic replacement of corticosteroids, and wean patient off of the opioid. (5.7)
- Severe Hypotension: Monitor during dosage initiation and titration. Avoid use of Hydromorphone Hydrochloride Tablets in patients with circulatory shock. (5.8)
- Risks of Use in Patients with Increased Intracranial Pressure, Brain Tumors, Head Injury, or Impaired Consciousness: Monitor for sedation and respiratory depression. Avoid use of Hydromorphone Hydrochloride Tablets in patients with impaired consciousness or coma. (5.9)

6 ADVERSE REACTIONS

Most common adverse reactions are lightheadedness, dizziness, sedation, nausea, vomiting, sweating, flushing, dysphoria, euphoria, dry mouth, and pruritus.

To report Suspected Adverse Reactions, contact Ascent Pharmaceuticals Inc. at 1-855-221-1622 or FDA at 1-800-FDA-1088 or www.fda.gov/medwatch.

7 DRUG INTERACTIONS

- Serotonergic Drugs: Concomitant use may result in serotonin syndrome. Discontinue Hydromorphone Hydrochloride Tablets. if serotonin syndrome is suspected. (7)
- Monoamine Oxidase Inhibitors (MAOIs): Can potentiate the effects of hydromorphone. Avoid concomitant use in patients receiving MAOIs or within 14 days of stopping treatment with an MAOI. (7)
- MixedAgonist/Antagonist and Partial Agonist Opioid Analgesics: Avoid use with Hydromorphone Hydrochloride because they may reduce analgesic effect of Hydromorphone Hydrochloride or precipitate withdrawal symptoms. (7)

8 USE IN SPECIFIC POPULATIONS

- Pregnancy: May cause fetal harm. (8.1)

FULL PRESCRIBING INFORMATION

WARNING: RISK OF MEDICATION ERRORS; ADDICTION, ABUSE, AND MISUSE; LIFE-THREATENING RESPIRATORY DEPRESSION; ACCIDENTAL INGESTION; NEONATAL OPIOID WITHDRAWAL SYNDROME; and RISKS FROM CONCOMITANT USE WITH BENZODIAZEPINES OR OTHER CNS DEPRESSANTS

Addiction, Abuse, and Misuse

Hydromorphone Hydrochloride Tablets expose patients and other users to the risks of opioid addiction, abuse, and misuse, which can lead to overdose and death. Assess each patient’s risk prior to prescribing Hydromorphone Hydrochloride Tablets, and monitor all patients regularly for the development of these behaviors and conditions [see Warnings and Precautions (5.2)].

Life-Threatening Respiratory Depression

Serious, life-threatening, or fatal respiratory depression may occur with use of Hydromorphone Hydrochloride Tablets. Monitor for respiratory depression, especially during initiation of Hydromorphone Hydrochloride Tablets or following a dose increase [see Warnings and Precautions (5.3)].

Accidental Ingestion

Accidental ingestion of even one dose of Hydromorphone Hydrochloride Tablets, especially by children, can result in a fatal overdose of hydromorphone [see Warnings and Precautions (5.3)].

Neonatal Opioid Withdrawal Syndrome

Prolonged use of Hydromorphone Hydrochloride Tablets during pregnancy can result in neonatal opioid withdrawal syndrome, which may be life-threatening if not recognized and treated, and requires management according to protocols developed by neonatology experts. If opioid use is required for a prolonged period in a pregnant woman, advise the patient of the risk of neonatal opioid withdrawal syndrome and ensure that appropriate treatment will be available [see Warnings and Precautions (5.4].

Risks From Concomitant Use With Benzodiazepines Or Other CNS Depressants

Concomitant use of opioids with benzodiazepines or other central nervous system (CNS) depressants, including alcohol, may result in profound sedation, respiratory depression, coma, and death [see Warnings and Precautions (5.5), Drug Interactions (7)].

- Reserve concomitant prescribing of Hydromorphone Hydrochloride Tablets and benzodiazepines or other CNS depressants for use in patients for whom alternative treatment options are inadequate.
- Limit dosages and durations to the minimum required.
- Follow patients for signs and symptoms of respiratory depression and sedation.

1 INDICATIONS AND USAGE

Hydromorphone Hydrochloride Tablets are indicated for the management of pain severe enough to require an opioid analgesic and for which alternative treatments are inadequate.

Limitations of Use

Because of the risks of addiction, abuse, and misuse with opioids, even at recommended doses [see Warnings and Precautions (5.2)], reserve Hydromorphone Hydrochloride Tablets for use in patients for whom alternative treatment options [e.g., non-opioid analgesics or opioid combination products]:

- Have not been tolerated, or are not expected to be tolerated,
- Have not provided adequate analgesia, or are not expected to provide adequate analgesia

2 DOSAGE AND ADMINISTRATION

2.1 Important Dosage and Administration Instructions

- Use the lowest effective dosage for the shortest duration consistent with individual patient treatment goals [see Warnings and Precautions (5)].

- Initiate the dosing regimen for each patient individually, taking into account the patient's severity of pain, patient response, prior analgesic treatment experience, and risk factors for addiction, abuse, and misuse [see Warnings and Precautions (5.2)].
- Monitor patients closely for respiratory depression, especially within the first 24-72 hours of initiating therapy and following dosage increases with Hydromorphone Hydrochloride Tablets and adjust the dosage accordingly [see Warnings and Precautions (5.3)].

2.2 Initial Dosage

Initiating Treatment with Hydromorphone Hydrochloride Tablets

Hydromorphone Hydrochloride Tablets

Initiate treatment with Hydromorphone Hydrochloride Tablets in a dosing range of 2 mg to 4 mg, orally, every 4 to 6 hours.

Conversion from Other Opioids to Hydromorphone Hydrochloride Tablets

There is inter-patient variability in the potency of opioid drugs and opioid formulations. Therefore, a conservative approach is advised when determining the total daily dosage of Hydromorphone Hydrochloride Tablets. It is safer to underestimate a patient’s 24-hour Hydromorphone Hydrochloride dosage than to overestimate the 24-hour dosage and manage an adverse reaction due to overdose.

In general, it is safest to start Hydromorphone Hydrochloride therapy by administering half of the usual starting dose every 4-6 hours for Hydromorphone Hydrochloride Tablets. The dose of Hydromorphone Hydrochloride can be gradually adjusted until adequate pain relief and acceptable side effects have been achieved [See Dosage and Administration (2.4)].

Conversion from Hydromorphone Hydrochloride Tablets to Extended-Release Hydromorphone Hydrochloride

The relative bioavailability of Hydromorphone Hydrochloride Tablets compared to extended-release Hydromorphone Hydrochloride is unknown, so conversion to extended-release tablets must be accompanied by close observation for signs of excessive sedation and respiratory depression.

2.3 Dosage Modifications in Patients with Hepatic Impairment

Initiate treatment with one-fourth to one-half the usual Hydromorphone Hydrochloride starting dose depending on the degree of impairment [see Use in Specific Populations (8.6), and Clinical Pharmacology (12.3)].

2.4 Dosage Modifications in Patients with Renal Impairment

Initiate treatment with one-fourth to one-half the usual Hydromorphone Hydrochloride starting dose depending on the degree of impairment [see Use in Specific Populations (8.7), and Clinical Pharmacology (12.3)].

2.5 Titration and Maintenance of Therapy

Individually titrate Hydromorphone Hydrochloride Tablets to a dose that provides adequate analgesia and minimizes adverse reactions. Continually reevaluate patients receiving Hydromorphone Hydrochloride Tablets to assess the maintenance of pain control and the relative incidence of adverse reactions, as well as monitoring for the development of addiction, abuse, or misuse [see Warnings and Precautions (5.2]. Frequent communication is important among the prescriber, other members of the healthcare team, the patient, and the caregiver/family during periods of changing analgesic requirements, including initial titration.

If the level of pain increases after dosage stabilization, attempt to identify the source of increased pain before increasing the Hydromorphone Hydrochloride Tablets dosage. If unacceptable opioid-related adverse reactions are observed, consider reducing the dosage. Adjust the dosage to obtain an appropriate balance between management of pain and opioid-related adverse reactions.

For chronic pain, doses should be administered around-the-clock. A supplemental dose of 5-15% of the total daily usage may be administered every two hours on an as-needed basis.

2.6 Discontinuation of Hydromorphone Hydrochloride Tablets

When a patient who has been taking Hydromorphone Hydrochloride Tablets regularly and may be physically dependent no longer requires therapy with Hydromorphone Hydrochloride, taper the dose gradually, by 25% to 50% every 2 to 4 days, while monitoring carefully for signs and symptoms of withdrawal. If the patient develops these signs and symptoms, raise the dose to the previous level and taper more slowly, either by increasing the interval between decreases, decreasing the amount of change in dose, or both. Do not abruptly discontinue Hydromorphone Hydrochloride Tablets in a physically dependent patient. [see Warnings and Precautions (5.12), Drug Abuse and Dependence (9.3)].

3 DOSAGE FORMS AND STRENGTHS

Hydromorphone Hydrochloride Tablets, USP:

- 2 mg tablets (light orange, round, flat, beveled edge tablets, de-bossed with “T” on one side and “263” on other side.)
- 4 mg tablets (light yellow, round, flat, beveled edge tablets, de-bossed with “T” on one side and “264” on other side.)
- 8 mg tablets (white to off-white, round, flat, beveled edge tablets, de-bossed with a “T” and “265” with a break line on one side and plain on the other side)

4 CONTRAINDICATIONS

Hydromorphone Hydrochloride Tablets are contraindicated in patients with:

- Significant respiratory depression [see Warnings and Precautions (5.6)]
- Acute or severe bronchial asthma in an unmonitored setting or in the absence of resuscitative equipment [see Warnings and Precautions (5.6)]
- Known or suspected gastrointestinal obstruction, including paralytic ileus [see Warnings and Precautions (5.10)]
- Hypersensitivity to hydromorphone, hydromorphone salts, any other components of the product, or sulfite-containing medications (e.g., anaphylaxis) [see Warnings and Precautions (5.15;) Adverse Reactions (6.1)]

5 WARNINGS AND PRECAUTIONS

5.1 Risk of Accidental Overdose and Death due to Medication Errors

Dosing errors can result in accidental overdose and death. Ensure that the dose is communicated clearly and dispensed accurately. A household teaspoon or tablespoon is not an adequate measuring device. Given the inexactitude of the household spoon measure and the possibility of using a tablespoon instead of a teaspoon, which could lead to overdosage, the enclosed measuring device should be used or a calibrated measuring device obtained from the pharmacist. Health care providers should recommend a calibrated device that can measure and deliver the prescribed dose accurately, and instruct caregivers to use extreme caution in measuring the dosage.

5.2 Addiction, Abuse, and Misuse

Hydromorphone Hydrochloride Tablets contain hydromorphone, a Schedule II controlled substance. As an opioid, Hydromorphone Hydrochloride exposes users to the risks of addiction, abuse, and misuse [see Drug Abuse and Dependence (9)].

Although the risk of addiction in any individual is unknown, it can occur in patients appropriately prescribed Hydromorphone Hydrochloride Tablets. Addiction can occur at recommended dosages and if the drug is misused or abused.

Assess each patient’s risk for opioid addiction, abuse, or misuse prior to prescribing Hydromorphone Hydrochloride Tablets, and monitor all patients receiving Hydromorphone Hydrochloride Tablets for the development of these behaviors and conditions. Risks are increased in patients with a personal or family history of substance abuse (including drug or alcohol abuse or addiction) or mental illness (e.g., major depression). The potential for these risks should not, however, prevent the proper management of pain in any given patient. Patients at increased risk may be prescribed opioids such as Hydromorphone Hydrochloride Tablets, but use in such patients necessitates intensive counseling about the risks and proper use of Hydromorphone Hydrochloride Tablets along with intensive monitoring for signs of addiction, abuse, and misuse.

Opioids are sought by drug abusers and people with addiction disorders and are subject to criminal diversion. Consider these risks when prescribing or dispensing Hydromorphone Hydrochloride Tablets. Strategies to reduce these risks include prescribing the drug in the smallest appropriate quantity and advising the patient on the proper disposal of unused drug [see Patient Counseling Information (17)]. Contact local state professional licensing board or state controlled substances authority for information on how to prevent and detect abuse or diversion of this product.

5.3 Life-Threatening Respiratory Depression

Serious, life-threatening, or fatal respiratory depression has been reported with the use of opioids, even when used as recommended. Respiratory depression, if not immediately recognized and treated, may lead to respiratory arrest and death. Management of respiratory depression may include close observation, supportive measures, and use of opioid antagonists, depending on the patient’s clinical status [see Overdosage (10)]. Carbon dioxide (CO2) retention from opioid-induced respiratory depression can exacerbate the sedating effects of opioids.

While serious, life-threatening, or fatal respiratory depression can occur at any time during the use of Hydromorphone Hydrochloride Tablets, the risk is greatest during the initiation of therapy or following a dosage increase. Monitor patients closely for respiratory depression, especially within the first 24-72 hours of initiating therapy with and following dosage increases of Hydromorphone Hydrochloride Tablets.

To reduce the risk of respiratory depression, proper dosing and titration of Hydromorphone Hydrochloride Tablets are essential [see Dosage and Administration (2)].

Overestimating the Hydromorphone Hydrochloride Tablets dosage when converting patients from another opioid product can result in a fatal overdose with the first dose.

Accidental ingestion of even one dose of Hydromorphone Hydrochloride Tablets, especially by children, can result in respiratory depression and death due to an overdose of hydromorphone.

5.4 Neonatal Opioid Withdrawal Syndrome

Prolonged use of Hydromorphone Hydrochloride Tablets during pregnancy can result in withdrawal in the neonate. Neonatal opioid withdrawal syndrome, unlike opioid withdrawal syndrome in adults, may be life-threatening if not recognized and treated, and requires management according to protocols developed by neonatology experts. Observe newborns for signs of neonatal opioid withdrawal syndrome and manage accordingly. Advise pregnant women using opioids for a prolonged period of the risk of neonatal opioid withdrawal syndrome and ensure that appropriate treatment will be available [see Use in Specific Populations (8.1), Patient Counseling Information (17)].

5.5 Risks from Concomitant Use with Benzodiazepines or Other CNS Depressants

Profound sedation, respiratory depression, coma, and death may result from the concomitant use of Hydromorphone Hydrochloride Tablets with benzodiazepines or other CNS depressants (e.g., non-benzodiazepine sedatives/hypnotics, anxiolytics, tranquilizers, muscle relaxants, general anesthetics, antipsychotics, other opioids, alcohol). Because of these risks, reserve concomitant prescribing of these drugs for use in patients for whom alternative treatment options are inadequate.

Observational studies have demonstrated that concomitant use of opioid analgesics and benzodiazepines increases the risk of drug-related mortality compared to use of opioid analgesics alone. Because of similar pharmacological properties, it is reasonable to expect similar risk with the concomitant use of other CNS depressant drugs with opioid analgesics [see Drug Interactions (7)].

If the decision is made to prescribe a benzodiazepine or other CNS depressant concomitantly with an opioid analgesic, prescribe the lowest effective dosages and minimum durations of concomitant use. In patients already receiving an opioid analgesic, prescribe a lower initial dose of the benzodiazepine or other CNS depressant than indicated in the absence of an opioid, and titrate based on clinical response. If an opioid analgesic is initiated in a patient already taking a benzodiazepine or other CNS depressant, prescribe a lower initial dose of the opioid analgesic, and titrate based on clinical response. Follow patients closely for signs and symptoms of respiratory depression and sedation.

Advise both patients and caregivers about the risks of respiratory depression and sedation when Hydromorphone Hydrochloride Tablets are used with benzodiazepines or other CNS depressants (including alcohol and illicit drugs). Advise patients not to drive or operate heavy machinery until the effects of concomitant use of the benzodiazepine or other CNS depressant have been determined. Screen patients for risk of substance use disorders, including opioid abuse and misuse, and warn them of the risk for overdose and death associated with the use of additional CNS depressants including alcohol and illicit drugs [see Drug Interactions (7), Patient Counseling Information (17)]

5.6 Life-Threatening Respiratory Depression in Patients with Chronic Pulmonary Disease or in Elderly, Cachectic, or Debilitated Patients

The use of Hydromorphone Hydrochloride Tablets in patients with acute or severe bronchial asthma in an unmonitored setting or in the absence of resuscitative equipment is contraindicated.

Patients with Chronic Pulmonary Disease: Hydromorphone Hydrochloride Tablet- treated patients with significant chronic obstructive pulmonary disease or cor pulmonale, and those with a substantially decreased respiratory reserve, hypoxia, hypercapnia, or pre-existing respiratory depression are at increased risk of decreased respiratory drive including apnea, even at recommended dosages of Hydromorphone Hydrochloride Tablets [see Warnings and Precautions (5.3)].

Elderly, Cachectic, or Debilitated Patients: Life-threatening respiratory depression is more likely to occur in elderly, cachectic, or debilitated patients because they may have altered pharmacokinetics or altered clearance compared to younger, healthier patients [see Warnings and Precautions (5.3)].

Monitor such patients closely, particularly when initiating and titrating Hydromorphone Hydrochloride Tablets and when Hydromorphone Hydrochloride is given concomitantly with other drugs that depress respiration [see Warnings and Precautions (5.3)]. Alternatively, consider the use of non-opioid analgesics in these patients.

5.7 Adrenal Insufficiency

Cases of adrenal insufficiency have been reported with opioid use, more often following greater than one month of use. Presentation of adrenal insufficiency may include non-specific symptoms and signs including nausea, vomiting, anorexia, fatigue, weakness, dizziness, and low blood pressure. If adrenal insufficiency is suspected, confirm the diagnosis with diagnostic testing as soon as possible. If adrenal insufficiency is diagnosed, treat with physiologic replacement doses of corticosteroids. Wean the patient off of the opioid to allow adrenal function to recover and continue corticosteroid treatment until adrenal function recovers. Other opioids may be tried as some cases reported use of a different opioid without recurrence of adrenal insufficiency. The information available does not identify any particular opioids as being more likely to be associated with adrenal insufficiency.

5.8 Severe Hypotension

Hydromorphone Hydrochloride Tablets may cause severe hypotension including orthostatic hypotension and syncope in ambulatory patients. There is increased risk in patients whose ability to maintain blood pressure has already been compromised by a reduced blood volume or concurrent administration of certain CNS depressant drugs (e.g. phenothiazines or general anesthetics) [see Drug Interactions (7)]. Monitor these patients for signs of hypotension after initiating or titrating the dosage of Hydromorphone Hydrochloride Tablets. In patients with circulatory shock, Hydromorphone Hydrochloride may cause vasodilation that can further reduce cardiac output and blood pressure. Avoid the use of Hydromorphone Hydrochloride Tablets in patients with circulatory shock.

5.9 Risks of Use in Patients with Increased Intracranial Pressure, Brain Tumors, Head Injury, or Impaired Consciousness

In patients who may be susceptible to the intracranial effects of CO2 retention (e.g., those with evidence of increased intracranial pressure or brain tumors), Hydromorphone Hydrochloride Tablets may reduce respiratory drive, and the resultant CO2 retention can further increase intracranial pressure. Monitor such patients for signs of sedation and respiratory depression, particularly when initiating therapy with Hydromorphone Hydrochloride Tablets.

Opioids may also obscure the clinical course in a patient with a head injury. Avoid the use of Hydromorphone Hydrochloride in patients with impaired consciousness or coma.

5.10 Risks of Use in Patients with Gastrointestinal Conditions

Hydromorphone Hydrochloride Tablets are contraindicated in patients with known or suspected gastrointestinal obstruction, including paralytic ileus.

The hydromorphone in Hydromorphone Hydrochloride Tablets may cause spasm of the sphincter of Oddi. Opioids may cause increases in serum amylase. Monitor patients with biliary tract disease, including acute pancreatitis, for worsening symptoms.

5.11 Increased Risk of Seizures in Patients with Seizure Disorders

The hydromorphone in Hydromorphone Hydrochloride Tablets may increase the frequency of seizures in patients with seizure disorders, and may increase the risk of seizures occurring in other clinical settings associated with seizures. Monitor patients with a history of seizure disorders for worsened seizure control during Hydromorphone Hydrochloride Tablets therapy.

5.12 Withdrawal

Avoid the use of mixed agonist/antagonist (e.g., pentazocine, nalbuphine, and butorphanol) or partial agonist (e.g., buprenorphine) analgesics in patients who are receiving a full opioid agonist analgesic, including Hydromorphone Hydrochloride Tablets. In these patients, mixed agonist/antagonist and partial agonist analgesics may reduce the analgesic effect and/or precipitate withdrawal symptoms [see Drug Interactions (7)].

When discontinuing Hydromorphone Hydrochloride Tablets in a physically-dependent patient, gradually taper the dosage [see Dosage and Administration (2.6)]. Do not abruptly discontinue Hydromorphone Hydrochloride Tablets in these patients. [see Drug Abuse and Dependence (9.3)].

5.13 Risks of Driving and Operating Machinery

Hydromorphone Hydrochloride Tablets may impair the mental or physical abilities needed to perform potentially hazardous activities such as driving a car or operating machinery. Warn patients not to drive or operate dangerous machinery unless they are tolerant to the effects of Hydromorphone Hydrochloride Tablets and know how they will react to the medication.

5.14 Sulfites

Hydromorphone Hydrochloride Tablets contain sodium metabisulfite, a sulfite that may cause allergic-type reactions including anaphylactic symptoms and life-threatening or less severe asthmatic episodes in certain susceptible people. The overall prevalence of sulfite sensitivity in the general population is unknown and probably low. Sulfite sensitivity is seen more frequently in asthmatic than in nonasthmatic people. Use of Hydromorphone Hydrochloride Tablets is contraindicated in patients with hypersensitivity to sulfite-containing medications.

6 ADVERSE REACTIONS

The following serious adverse reactions are described, or described in greater detail, in other sections:

- Addiction, Abuse, and Misuse [see Warnings and Precautions (5.2)]
- Life-Threatening Respiratory Depression [see Warnings and Precautions (5.3)]
- Neonatal Opioid Withdrawal Syndrome [see Warnings and Precautions (5.4)]
- Interactions with Benzodiazepines or Other CNS Depressants [see Warnings and Precautions (5.5)
- Adrenal Insufficiency [see Warnings and Precautions (5.7)]
- Severe Hypotension [see Warnings and Precautions (5.8)]
- Gastrointestinal Adverse Reactions [see Warnings and Precautions (5.10)]
- Seizures [see Warnings and Precautions (5.11)]
- Withdrawal [see Warnings and Precautions (5.12]

6.1 Clinical Trial Experience

undefined

6.2 Postmarketing Experience

The following adverse reactions have been identified during post approval use of hydromorphone. Because these reactions are reported voluntarily from a population of uncertain size, it is not always possible to reliably estimate their frequency or establish a causal relationship to drug exposure.

Confusional state, convulsions, drowsiness, dyskinesia, dyspnea, erectile dysfunction, fatigue, hepatic enzymes increased, hyperalgesia, hypersensitivity reaction, lethargy, myoclonus, oropharyngeal swelling, peripheral edema, and somnolence.

Serotonin syndrome: Cases of serotonin syndrome, a potentially life-threatening condition, have been reported during concomitant use of opioids with serotonergic drugs.

Adrenal insufficiency: Cases of adrenal insufficiency have been reported with opioid use, more often following greater than one month of use.

Anaphylaxis: Anaphylaxis has been reported with ingredients contained in Hydromorphone Hydrochloride Tablets

Androgen deficiency: Cases of androgen deficiency have occurred with chronic use of opioids

[see Clinical Pharmacology (12.2)].

7 DRUG INTERACTIONS

Table 1 includes clinically significant drug interactions with Hydromorphone Hydrochloride.

Table 1: Clinically Significant Drug Interactions with Hydromorphone Hydrochloride

Benzodiazepines and other Central Nervous System (CNS) Depressants
Clinical Impact: | Due to additive pharmacologic effect, the concomitant use of benzodiazepines or other CNS depressants, including alcohol, can increase the risk of hypotension, respiratory depression, profound sedation, coma, and death.
Intervention: | Reserve concomitant prescribing of these drugs for use in patients for whom alternative treatment options are inadequate. Limit dosages and durations to the minimum required. Follow patients closely for signs of respiratory depression and sedation [see Warnings and Precautions (5.X)].
Examples: | Benzodiazepines and other sedatives/hypnotics, anxiolytics, tranquilizers, muscle relaxants, general anesthetics, antipsychotics, other opioids, alcohol.
Serotonergic Drugs
Clinical Impact: | The concomitant use of opioids with other drugs that affect the serotonergic neurotransmitter system has resulted in serotonin syndrome
Intervention: | If concomitant use is warranted, carefully observe the patient, particularly during treatment initiation and dose adjustment. Discontinue Hydromorphone Hydrochloride Tablets if serotonin syndrome is suspected.
Examples: | Selective serotonin reuptake inhibitors (SSRIs), serotonin and norepinephrine reuptake inhibitors (SNRIs), tricyclic antidepressants (TCAs), triptans, 5-HT3 receptor antagonists, drugs that affect the serotonin neurotransmitter system (e.g., mirtazapine, trazodone, tramadol), monoamine oxidase (MAO) inhibitors (those intended to treat psychiatric disorders and also others, such as linezolid and intravenous methylene blue).
Monoamine Oxidase Inhibitors (MAOIs)
Clinical Impact: | MAOI interactions with opioids may manifest as serotonin syndrome or opioid
 | toxicity (e.g., respiratory depression, coma) [see Warnings and Precautions (5.3)].; If urgent use of an opioid is necessary, use test doses and frequent titration of small doses to treat pain while closely monitoring blood pressure and signs and symptoms of CNS and respiratory depression.
Intervention: | The use of Hydromorphone Hydrochloride Tablets is not recommended for patients taking MAOIs or within 14 days of stopping such treatment.
Examples: | phenelzine, tranylcypromine, linezolid
Mixed Agonist/Antagonist and Partial Agonist Opioid Analgesics
Clinical Impact: | May reduce the analgesic effect of Hydromorphone Hydrochloride Tablets and/or precipitate withdrawal symptoms.
Intervention: | Avoid concomitant use.
Examples: | butorphanol, nalbuphine, pentazocine, buprenorphine,
Muscle Relaxants
Clinical Impact: | Hydromorphone may enhance the neuromuscular blocking action of skeletal muscle relaxants and produce an increased degree of respiratory depression.
Intervention: | Monitor patients for signs of respiratory depression that may be greater than otherwise expected and decrease the dosage of Hydromorphone Hydrochloride Tablets and/or the muscle relaxant as necessary.
Diuretics
Clinical Impact: | Opioids can reduce the efficacy of diuretics by inducing the release of antidiuretic hormone.
Intervention: | Monitor patients for signs of diminished diuresis and/or effects on blood pressure and increase the dosage of the diuretic as needed.
Anticholinergic Drugs
Clinical Impact: | The concomitant use of anticholinergic drugs may increase risk of urinary retention and/or severe constipation, which may lead to paralytic ileus.
Intervention: | Monitor patients for signs of urinary retention or reduced gastric motility when Hydromorphone Hydrochloride Tablets is used concomitantly with anticholinergic drugs.

8 USE IN SPECIFIC POPULATIONS

8.1 Pregnancy

Risk Summary

Prolonged use of opioid analgesics during pregnancy may cause neonatal opioid withdrawal syndrome [see Warnings and Precautions (5.4)]. There are no available data with Hydromorphone Hydrochloride in pregnant women to inform a drug-associated risk for major birth defects and miscarriage.

In animal reproduction studies, reduced postnatal survival of pups, and decreased were noted following oral treatment of pregnant rats with hydromorphone during gestation and through lactation at doses 0.8 times the human daily dose of 24 mg/day (HDD), respectively. In published studies, neural tube defects were noted following subcutaneous injection of hydromorphone to pregnant hamsters at doses 6.4 times the HDD and soft tissue and skeletal abnormalities were noted following subcutaneous continuous infusion of 3 times the HDD to pregnant mice. No malformations were noted at 4 or 40.5 times the HDD in pregnant rats or rabbits, respectively [see Data]. Based on animal data, advise pregnant women of the potential risk to a fetus.

The estimated background risk of major birth defects and miscarriage for the indicated population is unknown. All pregnancies have a background risk of birth defect, loss, or other adverse outcomes. In the U.S. general population, the estimated background risk of major birth defects and miscarriage in clinically recognized pregnancies is 2-4% and 15-20%, respectively.

Clinical Considerations

Fetal/Neonatal Adverse Reactions

Prolonged use of opioid analgesics during pregnancy for medical or nonmedical purposes can result in physical dependence in the neonate and neonatal opioid withdrawal syndrome shortly after birth.

Neonatal opioid withdrawal syndrome presents as irritability, hyperactivity and abnormal sleep pattern, high pitched cry, tremor, vomiting, diarrhea and failure to gain weight. The onset, duration, and severity of neonatal opioid withdrawal syndrome vary based on the specific opioid used, duration of use, timing and amount of last maternal use, and rate of elimination of the drug by the newborn. Observe newborns for symptoms of neonatal opioid withdrawal syndrome and manage accordingly [see Warnings and Precautions (5.4)].

Labor or Delivery

Opioids cross the placenta and may produce respiratory depression and psycho-physiologic effects in neonates. An opioid antagonist, such as naloxone, must be available for reversal of opioid-induced respiratory depression in the neonate. Hydromorphone Hydrochloride Tablets is not recommended for use in pregnant women during or immediately prior to labor, when other analgesic techniques are more appropriate. Opioid analgesics, including Hydromorphone Hydrochloride Tablets, can prolong labor through actions which temporarily reduce the strength, duration, and frequency of uterine contractions. However, this effect is not consistent and may be offset by an increased rate of cervical dilation, which tends to shorten labor. Monitor neonates exposed to opioid analgesics during labor for signs of excess sedation and respiratory depression.

Data

Animal Data

Pregnant rats were treated with Hydromorphone Hydrochloride from Gestation Day 6 to 17 via oral gavage doses of 1, 5, or 10 mg/kg/day (0.4, 2, or 4 times the HDD of 24 mg based on body surface area, respectively). Maternal toxicity was noted in all treatment groups (reduced food consumption and body weights in the two highest dose groups). There was no evidence of malformations or embryotoxicity reported.

Pregnant rabbits were treated with Hydromorphone Hydrochloride from Gestation Day 7 to 19 via oral gavage doses of 10, 25, or 50 mg/kg/day (8.1, 20.3, or 40.5 times the HDD of 24 mg based on body surface area, respectively). Maternal toxicity was noted in the two highest dose groups (reduced food consumption and body weights). There was no evidence of malformations or embryotoxicity reported.

In a published study, neural tube defects (exencephaly and cranioschisis) were noted following subcutaneous administration of Hydromorphone Hydrochloride (19 to 258 mg/kg) on Gestation Day 8 to pregnant hamsters (6.4 to 87.2 times the HDD of 24 mg/day based on body surface area). The findings cannot be clearly attributed to maternal toxicity. No neural tube defects were noted at 14 mg/kg (4.7 times the human daily dose of 24 mg/day).

In a published study, CF-1 mice were treated subcutaneously with continuous infusion of 7.5, 15, or 30 mg/kg/day Hydromorphone Hydrochloride (1.5, 3, or 6.1 times the human daily dose of 24 mg based on body surface area) via implanted osmotic pumps during organogenesis (Gestation Days 7 to 10). Soft tissue malformations (cryptorchidism, cleft palate, malformed ventricles and retina), and skeletal variations (split supraoccipital, checkerboard and split sternebrae, delayed ossification of the paws and ectopic ossification sites) were observed at doses 3 times the human dose of 24 mg/day based on body surface area. The findings cannot be clearly attributed to maternal toxicity.

Increased pup mortality and decreased pup body weights were noted at 0.8 and 2 times the human daily dose of 24 mg in a study in which pregnant rats were treated with Hydromorphone Hydrochloride from Gestation Day 7 to Lactation Day 20 via oral gavage doses of 0, 0.5, 2, or 5 mg/kg/day (0.2, 0.8, or 2 times the HDD of 24 mg based on body surface area, respectively). Maternal toxicity (decreased food consumption and body weight gain) was also noted at the two highest doses tested.

8.2 Lactation

Risk Summary

Low levels of opioid analgesics have been detected in human milk. The developmental and health benefits of breastfeeding should be considered along with the mother’s clinical need for Hydromorphone Hydrochloride Tablets and any potential adverse effects on the breastfed infant from Hydromorphone Hydrochloride Tablets or from the underlying maternal condition.

Clinical Considerations

Monitor infants exposed to Hydromorphone Hydrochloride through breast milk for excess sedation and respiratory depression. Withdrawal symptoms can occur in breastfed infants when maternal administration of hydromorphone is stopped, or when breast-feeding is stopped.

8.3 Females and Males of Reproductive Potential

Infertility

Chronic use of opioids may cause reduced fertility in females and males of reproductive potential. It is not known whether these effects on fertility are reversible [see Adverse Reactions (6.2), Clinical Pharmacology (12.2), Nonclinical Toxicology (13.1)].

8.4 Pediatric Use

The safety and effectiveness of Hydromorphone Hydrochloride in pediatric patients have not been established.

8.5 Geriatric Use

Elderly patients (aged 65 years or older) may have increased sensitivity to hydromorphone. In general, use caution when selecting a dosage for an elderly patient, usually starting at the low end of the dosing range, reflecting the greater frequency of decreased hepatic, renal, or cardiac function and of concomitant disease or other drug therapy.

Respiratory depression is the chief risk for elderly patients treated with opioids, and has occurred after large initial doses were administered to patients who were not opioid-tolerant or when opioids were co-administered with other agents that depress respiration. Titrate the dosage of Hydromorphone Hydrochloride slowly in geriatric patients and monitor closely for signs of central nervous system and respiratory depression [see Warnings and Precautions (5.6)].

Hydromorphone is known to be substantially excreted by the kidney, and the risk of adverse reactions to this drug may be greater in patients with impaired renal function. Because elderly patients are more likely to have decreased renal function, care should be taken in dose selection, and it may be useful to monitor renal function.

8.6 Hepatic Impairment

The pharmacokinetics of hydromorphone is affected by hepatic impairment. Due to increased exposure of hydromorphone, patients with hepatic impairment should be started at one-fourth to one-half the recommended starting dose depending on the degree of hepatic dysfunction and closely monitored during dose titration. The pharmacokinetics of hydromorphone in patients with severe hepatic impairment has not been studied. A further increase in Cmax and AUC of hydromorphone in this group is expected and should be taken into consideration when selecting a starting dose [see Clinical Pharmacology (12.3)].

8.7 Renal Impairment

The pharmacokinetics of hydromorphone is affected by renal impairment. In addition, in patients with severe renal impairment, hydromorphone appeared to be more slowly eliminated with a longer terminal elimination half-life. Start patients with renal impairment on one-fourth to one- half the usual starting dose depending on the degree of impairment. Patients with renal impairment should be closely monitored during dose titration [see Clinical Pharmacology (12.3)].

9 DRUG ABUSE AND DEPENDENCE

9.1 Controlled Substance

Hydromorphone Hydrochloride Tablets contain hydromorphone, a Schedule II controlled substance.

9.2 Abuse

Hydromorphone Hydrochloride Tablets contain hydromorphone, a substance with a high potential for abuse similar to other opioids including fentanyl, hydrocodone, oxycodone, methadone, morphine, oxymorphone and tapentadol. Hydromorphone Hydrochloride Tablets can be abused and is subject to misuse, addiction, and criminal diversion [see Warnings and Precautions (5.2)].

All patients treated with opioids require careful monitoring for signs of abuse and addiction, because use of opioid analgesic products carries the risk of addiction even under appropriate medical use.

Prescription drug abuse is the intentional non-therapeutic use of a prescription drug, even once, for its rewarding psychological or physiological effects.

Drug addiction is a cluster of behavioral, cognitive, and physiological phenomena that develop after repeated substance use and includes: a strong desire to take the drug, difficulties in controlling its use, persisting in its use despite harmful consequences, a higher priority given to drug use than to other activities and obligations, increased tolerance, and sometimes a physical withdrawal.

“Drug-seeking” behavior is very common in persons with substance use disorders. Drug-seeking tactics include emergency calls or visits near the end of office hours, refusal to undergo appropriate examination, testing, or referral, repeated “loss” of prescriptions, tampering with prescriptions, and reluctance to provide prior medical records or contact information for other treating healthcare provider(s). “Doctor shopping” (visiting multiple prescribers to obtain additional prescriptions) is common among drug abusers and people suffering from untreated addiction. Preoccupation with achieving adequate pain relief can be appropriate behavior in a patient with poor pain control.

Abuse and addiction are separate and distinct from physical dependence and tolerance. Healthcare providers should be aware that addiction may not be accompanied by concurrent tolerance and symptoms of physical dependence in all addicts. In addition, abuse of opioids can occur in the absence of true addiction.

Hydromorphone Hydrochloride, like other opioids, can be diverted for non-medical use into illicit channels of distribution. Careful record-keeping of prescribing information, including quantity, frequency, and renewal requests, as required by state and federal law, is strongly advised.

Proper assessment of the patient, proper prescribing practices, periodic re-evaluation of therapy, and proper dispensing and storage are appropriate measures that help to limit abuse of opioid drugs.

Risks Specific to Abuse of Hydromorphone Hydrochloride

Hydromorphone Hydrochloride Tablets are for oral use only. Abuse of Hydromorphone Hydrochloride Tablets poses a risk of overdose and death. The risk is increased with concurrent abuse of Hydromorphone Hydrochloride Tablets with alcohol and other central nervous system depressants.

Parenteral drug abuse is commonly associated with transmission of infectious diseases such as hepatitis and HIV.

9.3 Dependence

Both tolerance and physical dependence can develop during chronic opioid therapy. Tolerance is the need for increasing doses of opioids to maintain a defined effect such as analgesia (in the absence of disease progression or other external factors). Tolerance may occur to both the desired and undesired effects of drugs, and may develop at different rates for different effects.

Physical dependence results in withdrawal symptoms after abrupt discontinuation or a significant dosage reduction of a drug. Withdrawal also may be precipitated through the administration of drugs with opioid antagonist activity (e.g., naloxone, nalmefene), mixed agonist/antagonist analgesics (e.g., pentazocine, butorphanol, nalbuphine), or partial agonists (e.g., buprenorphine). Physical dependence may not occur to a clinically significant degree until after several days to weeks of continued opioid usage.

Hydromorphone Hydrochloride Tablets should not be abruptly discontinued in a physically-dependent patient [see Dosage and Administration (2.6)]. If Hydromorphone Hydrochloride Tablets are abruptly discontinued in a physically-dependent patient, a withdrawal syndrome may occur. Some or all of the following can characterize this syndrome: restlessness, lacrimation, rhinorrhea, yawning, perspiration, chills, myalgia, and mydriasis. Other signs and symptoms also may develop, including irritability, anxiety, backache, joint pain, weakness, abdominal cramps, insomnia, nausea, anorexia, vomiting, diarrhea, or increased blood pressure, respiratory rate, or heart rate.

Infants born to mothers physically dependent on opioids will also be physically dependent and may exhibit respiratory difficulties and withdrawal signs [see Use in Specific Populations (8.1)].

10 OVERDOSAGE

Clinical Presentation

Acute overdose with Hydromorphone Hydrochloride Tablets can be manifested by respiratory depression, somnolence progressing to stupor or coma, skeletal muscle flaccidity, cold and clammy skin, constricted pupils, and, in some cases, pulmonary edema, bradycardia, hypotension, partial or complete airway obstruction, atypical snoring, and death. Marked mydriasis rather than miosis may be seen with hypoxia in overdose situations [see Clinical Pharmacology (12.2)].

Treatment of Overdose

In case of overdose, priorities are the reestablishment of a patent and protected airway and institution of assisted or controlled ventilation, if needed. Employ other supportive measures (including oxygen and vasopressors) in the management of circulatory shock and pulmonary edema as indicated. Cardiac arrest or arrhythmias will require advanced life-support techniques.

The opioid antagonists, naloxone or nalmefene, are specific antidotes to respiratory depression resulting from opioid overdose. For clinically significant respiratory or circulatory depression secondary to hydromorphone overdose, administer an opioid antagonist. Opioid antagonists should not be administered in the absence of clinically significant respiratory or circulatory depression secondary to hydromorphone overdose.

Because the duration of opioid reversal is expected to be less than the duration of action of hydromorphone in Hydromorphone Hydrochloride Tablets, carefully monitor the patient until spontaneous respiration is reliably reestablished. If the response to an opioid antagonist is suboptimal or only brief in nature, administer additional antagonist as directed by the product’s prescribing information.

In an individual physically dependent on opioids, administration of the recommended usual dosage of the antagonist will precipitate an acute withdrawal syndrome. The severity of the withdrawal symptoms experienced will depend on the degree of physical dependence and the dose of the antagonist administered. If a decision is made to treat serious respiratory depression in the physically dependent patient, administration of the antagonist should be initiated with care and by titration with smaller than usual doses of the antagonist.

11 DESCRIPTION

Hydromorphone Hydrochloride, USP, a hydrogenated ketone of morphine, is an opioid agonist.

Hydromorphone Hydrochloride Tablets, USP are supplied in 2 mg, 4 mg, and 8 mg tablets for oral administration. The tablet strengths describe the amount of Hydromorphone Hydrochloride in each tablet.

The chemical name is 4,5α-epoxy-3-hydroxy-17-methylmorphinan-6-one hydrochloride. The molecular Weight is 321.80. Its molecular formula is C17H19NO3·HCl, and it has the following chemical structure:

Hydromorphone Hydrochloride, USP is a white or almost white crystalline powder that is freely soluble in water, sparingly soluble in alcohol, practically insoluble in ether.

The 2 mg, 4 mg, and 8 mg tablets contain the following inactive ingredients: lactose anhydrous, microcrystalline cellulose and magnesium stearate. Hydromorphone Hydrochloride Tablets, USP may also contain traces of sodium metabisulfite.

The 2 mg tablets also contain D&C red #30 Lake dye, and D&C yellow #10.

The 4 mg tablets also contain D&C yellow #10.

12 CLINICAL PHARMACOLOGY

12.1 Mechanism of Action

Hydromorphone is a full opioid agonist and is relatively selective for the mu-opioid receptor, although it can bind to other opioid receptors at higher doses. The principal therapeutic action of hydromorphone is analgesia. Like all full opioid agonists, there is no ceiling effect for analgesia with morphine. Clinically, dosage is titrated to provide adequate analgesia and may be limited by adverse reactions, including respiratory and CNS depression.

The precise mechanism of the analgesic action is unknown. However, specific CNS opioid receptors for endogenous compounds with opioid-like activity have been identified throughout the brain and spinal cord and are thought to play a role in the analgesic effects of this drug.

12.2 Pharmacodynamics

Effects on the Central Nervous System

Hydromorphone produces respiratory depression by direct action on brain stem respiratory centers. The respiratory depression involves a reduction in the responsiveness of the brain stem respiratory centers to both increases in carbon dioxide tension and to electrical stimulation.

Hydromorphone causes miosis, even in total darkness. Pinpoint pupils are a sign of opioid overdose but are not pathognomonic (e.g., pontine lesions of hemorrhagic or ischemic origins may produce similar findings). Marked mydriasis rather than miosis may be seen due to hypoxia in overdose situations.

Effects on the Gastrointestinal Tract and Other Smooth Muscle

Hydromorphone causes a reduction in motility associated with an increase in smooth muscle tone in the antrum of the stomach and duodenum. Digestion of food in the small intestine is delayed and propulsive contractions are decreased. Propulsive peristaltic waves in the colon are decreased, while tone may be increased to the point of spasm, resulting in constipation. Other opioid-induced effects may include a reduction in biliary and pancreatic secretions, spasm of sphincter of Oddi, and transient elevations in serum amylase.

Effects on the Cardiovascular System

Hydromorphone produces peripheral vasodilation which may result in orthostatic hypotension or syncope. Manifestations of histamine release and/or peripheral vasodilation may include pruritus, flushing, red eyes and sweating and/or orthostatic hypotension.

Effects on the Endocrine System

Opioids inhibit the secretion of adrenocorticotropic hormone (ACTH), cortisol, and luteinizing hormone (LH) in humans [see Adverse Reactions (6.2)]. They also stimulate prolactin, growth hormone (GH) secretion, and pancreatic secretion of insulin and glucagon.

Chronic use of opioids may influence the hypothalamic-pituitary-gonadal axis, leading to androgen deficiency that may manifest as low libido, impotence, erectile dysfunction, amenorrhea, or infertility. The causal role of opioids in the clinical syndrome of hypogonadism is unknown because the various medical, physical, lifestyle, and psychological stressors that may influence gonadal hormone levels have not been adequately controlled for in studies conducted to date [see Adverse Reactions (6.2)].

Effects on the Immune System

Opioids have been shown to have a variety of effects on components of the immune system in in vitro and animal models. The clinical significance of these findings is unknown. Overall, the effects of opioids appear to be modestly immunosuppressive.

Concentration–Efficacy Relationships

The minimum effective analgesic concentration will vary widely among patients, especially among patients who have been previously treated with potent agonist opioids. The minimum effective analgesic concentration of hydromorphone for any individual patient may increase over time due to an increase in pain, the development of a new pain syndrome, and/or the development of analgesic tolerance [see Dosage and Administration (2.1, 2.5)].

Concentration–Adverse Reaction Relationships

There is a relationship between increasing hydromorphone plasma concentration and increasing frequency of dose-related opioid adverse reactions such as nausea, vomiting, CNS effects, and respiratory depression. In opioid-tolerant patients, the situation may be altered by the development of tolerance to opioid-related adverse reactions [see Dosage and Administration (2.2, 2.3, 2.5)].

12.3 Pharmacokinetics

Absorption

The analgesic activity of Hydromorphone Hydrochloride (Hydromorphone Hydrochloride) is due to the parent drug, hydromorphone. Hydromorphone is rapidly absorbed from the gastrointestinal tract after oral administration and undergoes extensive first-pass metabolism. Exposure of hydromorphone (Cmax and AUC0-24) is dose-proportional at a dose range of 2 and 8 mg. In vivo bioavailability following single-dose administration of the 8 mg tablet is approximately 24% (coefficient of variation 21%). Bioequivalence between the Hydromorphone Hydrochloride 8 mg TABLET and an equivalent dose of Hydromorphone Hydrochloride Oral Solution has been demonstrated.

After oral administration of Hydromorphone Hydrochloride, peak plasma hydromorphone concentrations are generally attained within ½ to 1-hour.

Mean (%cv)
Dosage Form | Cmax; (ng) | Tmax; (hrs) | AUC; (ng*hr/mL) | T½; (hrs)
8 mg Tablet | 5.5 (33%) | 0.74 (34%) | 23.7 (28%) | 2.6 (18%)
8 mg Oral Liquid | 5.7 (31%) | 0.73 (71%) | 24.6 (29%) | 2.8 (20%)

Food Effects

In a study conducted with a single 8 mg dose of hydromorphone (2 mg hydromorphone immediate-release tablets), food lowered Cmax by 25%, prolonged Tmax by 0.8 hour, and increased AUC by 35%. The effects may not be clinically relevant.

Distribution

At therapeutic plasma levels, hydromorphone is approximately 8-19% bound to plasma proteins. After an intravenous bolus dose, the steady state of volume distribution [mean (% cv)] is 302.9 (32%) liters.

Elimination

The systemic clearance is approximately 1.96 (20%) liters/minute. The terminal elimination half- life of hydromorphone after an intravenous dose is about 2.3 hours.

Metabolism

Hydromorphone is extensively metabolized via glucuronidation in the liver, with greater than 95% of the dose metabolized to hydromorphone-3-glucuronide along with minor amounts of 6-hydroxy reduction metabolites.

Excretion

Only a small amount of the hydromorphone dose is excreted unchanged in the urine. Most of the dose is excreted as hydromorphone-3-glucuronide along with minor amounts of 6- hydroxy reduction metabolites.

Specific Populations

Hepatic Impairment

After oral administration of a single 4 mg dose (2 mg hydromorphone immediate-release tablets), mean exposure to hydromorphone (Cmax and AUC∞) is increased 4-fold in patients with moderate (Child-Pugh Group B) hepatic impairment compared with subjects with normal hepatic function. Due to increased exposure of hydromorphone, patients with moderate hepatic impairment should be started at a lower dose and closely monitored during dose titration. Pharmacokinetics of hydromorphone in severe hepatic impairment patients has not been studied. Further increase in Cmax and AUC of hydromorphone in this group is expected. As such, starting dose should be even more conservative [see Use in Specific Populations (8.6)].

Renal Impairment

After oral administration of a single 4 mg dose (2 mg hydromorphone immediate-release tablets), exposure to hydromorphone (Cmax and AUC0-48) is increased in patients with impaired renal function by 2-fold in moderate (CLcr = 40 - 60 mL/min) and 3-fold in severe (CLcr < 30 mL/min) renal impairment compared with normal subjects (CLcr > 80 mL/min). In addition, in patients with severe renal impairment hydromorphone appeared to be more slowly eliminated with longer terminal elimination half-life (40 hr) compared to patients with normal renal function (15 hr). Patients with moderate renal impairment should be started on a lower dose. Starting doses for patients with severe renal impairment should be even lower.

Patients with renal impairment should be closely monitored during dose titration [see Use in Specific Populations (8.7)].

Age: Geriatric Population

In the geriatric population, age has no effect on the pharmacokinetics of hydromorphone.

Sex

Sex has little effect on the pharmacokinetics of hydromorphone. Females appear to have higher Cmax (25%) than males with comparable AUC0-24 values. The difference observed in Cmax may not be clinically relevant.

13 NONCLINICAL TOXICOLOGY

13.1 Carcinogenesis, Mutagenesis, Impairment of Fertility

Carcinogenesis

Long term studies in animals to evaluate the carcinogenic potential of hydromorphone have not been conducted.

Mutagenesis

Hydromorphone was positive in the mouse lymphoma assay in the presence of metabolic activation, but was negative in the mouse lymphoma assay in the absence of metabolic activation. Hydromorphone was not mutagenic in the in vitro bacterial reverse mutation assay (Ames assay). Hydromorphone was not clastogenic in either the in vitro human lymphocyte chromosome aberration assay or the in vivo mouse micronucleus assay.

Impairment of Fertility

Reduced implantation sites and viable fetuses were noted at 2.1 times the human daily dose of 32 mg/day in a study in which female rats were treated orally with 1.75, 3.5, or 7 mg/kg/day Hydromorphone Hydrochloride (0.5, 1.1, or 2.1 times a human daily dose of 24 mg/day (HDD) based on body surface area) beginning 14 days prior to mating through Gestation Day 7 and male rats were treated with the same Hydromorphone Hydrochloride doses beginning 28 days prior to and throughout mating.

14 CLINICAL STUDIES

Analgesic effects of single doses of Hydromorphone Hydrochloride Oral Solution administered to patients with post-surgical pain have been studied in double-blind controlled trials. In one study, both 5 mg and 10 mg of Hydromorphone Hydrochloride Oral Solution provided significantly more analgesia than placebo. In another trial, 5 mg and 10 mg of Hydromorphone Hydrochloride Oral Solution were compared to 30 mg and 60 mg of morphine sulfate oral liquid. The pain relief provided by 5 mg and 10 mg Hydromorphone Hydrochloride Oral Solution was comparable to 30 mg and 60 mg oral morphine sulfate, respectively.

16 HOW SUPPLIED/STORAGE AND HANDLING

Hydromorphone Hydrochloride Tablets USP, 2 mg are light orange, round, flat, beveled edge tablets, de-bossed with “T” on one side and “263” on other side.

They are available in: Bottles of 30 - NDC # 43602-002-30

Bottles of 500 – NDC # 43602-002-05

Hydromorphone Hydrochloride Tablets USP, 4 mg are light yellow, round, flat, beveled edge tablets, de-bossed with “T” on one side and “264” on other side.

They are available in: Bottles of 30 - NDC # 43602-003-30

Bottles of 500 – NDC # 43602-003-05

Hydromorphone Hydrochloride Tablets USP, 8 mg are white to off-white, round, flat, beveled edge tablets, de-bossed with a “T” and “265” with a break line on one side and plain on the other side.

They are available in: Bottles of 30 - NDC # 43602-004-30

Bottles of 500 – NDC # 43602-004-05

Store at 20°C to 25°C (68°F to 77°F). [See USP Controlled Room Temperature]. Protect from light.

17 PATIENT COUNSELING INFORMATION

Advise the patient to read the FDA-approved patient labeling (Medication Guide).

Addiction, Abuse, and Misuse

Inform patients that the use of Hydromorphone Hydrochloride Tablets, even when taken as recommended, can result in addiction, abuse, and misuse, which can lead to overdose and death [see Warnings and Precautions (5.2)]. Instruct patients not to share Hydromorphone Hydrochloride Tablets with others and to take steps to protect Hydromorphone Hydrochloride Tablets from theft or misuse.

Life-Threatening Respiratory Depression

Inform patients of the risk of life-threatening respiratory depression, including information that the risk is greatest when starting Hydromorphone Hydrochloride Tablets or when the dosage is increased, and that it can occur even at recommended dosages [see Warnings and Precautions (5.3)]. Advise patients how to recognize respiratory depression and to seek medical attention if breathing difficulties develop.

Accidental Ingestion

Inform patients that accidental ingestion, especially by children, may result in respiratory depression or death [see Warnings and Precautions (5.3)]. Instruct patients to take steps to store Hydromorphone Hydrochloride Tablets securely and to dispose of unused Hydromorphone Hydrochloride Tablets. When Hydromorphone Hydrochloride Tablets are no longer needed, the unused medication should be destroyed by flushing it down the toilet.

Interactions with Benzodiazepines and Other CNS Depressants

Inform patients and caregivers that potentially fatal additive effects may occur if Hydromorphone Hydrochloride Tablets are used with benzodiazepines or other CNS depressants, including alcohol, and not to use these concomitantly unless supervised by a health care provider [see Warnings and Precautions (5.4), Drug Interactions (7)].

Serotonin Syndrome

Inform patients that Hydromorphone Hydrochloride could cause a rare but potentially life-threatening condition resulting from concomitant administration of serotonergic drugs. Warn patients of the symptoms of serotonin syndrome and to seek medical attention right away if symptoms develop. Instruct patients to inform their healthcare providers if they are taking, or plan to take serotonergic medications. [see Drug Interactions 7].

MAOI Interaction

Inform patients to avoid taking Hydromorphone Hydrochloride Tablets while using any drugs that inhibit monoamine oxidase. Patients should not start MAOIs while taking Hydromorphone Hydrochloride Tablets [see Dug Interactions (7)].

Adrenal Insufficiency

Inform patients that opioids could cause adrenal insufficiency, a potentially life-threatening condition. Adrenal insufficiency may present with non-specific symptoms and signs such as nausea, vomiting, anorexia, fatigue, weakness, dizziness, and low blood pressure. Advise patients to seek medical attention if they experience a constellation of these symptoms [see Warnings and Precautions (5.7)].

Important Administration Instructions

Instruct patients how to properly take Hydromorphone Hydrochloride.

- Advise patients not to adjust the dose of Hydromorphone Hydrochloride Tablets without consulting with a physician or other healthcare professional.
- If patients have been receiving treatment with Hydromorphone Hydrochloride Tablets for more than a few weeks and cessation of therapy is indicated, counsel them on the importance of safely tapering the dose as abrupt discontinuation of the medication could precipitate withdrawal symptoms. Provide a dose schedule to accomplish a gradual discontinuation of the medication [see Dosage and Administration (2.5, 2.6)].

Hypotension

Inform patients that Hydromorphone Hydrochloride Tablets may cause orthostatic hypotension and syncope. Instruct patients how to recognize symptoms of low blood pressure and how to reduce the risk of serious consequences should hypotension occur (e.g., sit or lie down, carefully rise from a sitting or lying position) [see Warnings and Precautions (5.8)].

Anaphylaxis

Inform patients that anaphylaxis has been reported with ingredients contained in Hydromorphone Hydrochloride Tablets. Advise patients how to recognize such a reaction and when to seek medical attention [see Contraindications (4), Adverse Reactions (6)].

Pregnancy

Neonatal Opioid Withdrawal Syndrome

Inform female patients of reproductive potential that prolonged use of Hydromorphone Hydrochloride Tablets during pregnancy can result in neonatal opioid withdrawal syndrome, which may be life-threatening if not recognized and treated [see Warnings and Precautions (5.4), Use in Specific Populations (8.1)].

Embryo-Fetal Toxicity

Inform female patients of reproductive potential that Hydromorphone Hydrochloride Tablets can cause fetal harm and to inform their healthcare provider of a known or suspected pregnancy [see Use in Specific Populations (8.1), Warnings and Precautions (5.4)]

Lactation

Advise nursing mothers to monitor infants for increased sleepiness (more than usual), breathing difficulties, or limpness. Instruct nursing mothers to seek immediate medical care if they notice these signs [see Use in Specific Populations (8.2)].

Infertility

Inform patients that chronic use of opioids may cause reduced fertility. It is not known whether these effects on fertility are reversible [see Use in Specific Population (8.3)].

Driving or Operating Heavy Machinery

Inform patients that Hydromorphone Hydrochloride Tablets may impair the ability to perform potentially hazardous activities such as driving a car or operating heavy machinery.

Advise patients not to perform such tasks until they know how they will react to the medication

[see Warnings and Precautions (5.13)].

Constipation

Advise patients of the potential for severe constipation, including management instructions and when to seek medical attention [see Adverse Reactions (6), Clinical Pharmacology (12.2)].

Disposal of Unused Hydromorphone Hydrochloride Tablets

Advise patients to flush unused Hydromorphone Hydrochloride Tablets down the toilet.

Healthcare professionals can telephone Ascent Pharmaceuticals Inc (1-855-221-1622) for information on this product.

Manufactured by:

Ascent Pharmaceuticals Inc.

Central Islip, NY 11722

Revised: 07/17

MEDICATION GUIDE

MedicationGuide

Hydromorphonehydrochloride (HYE-droe-MOR-fone HYE-droe-KLOR-ide)Tablets, CII

Hydromorphonehydrochloride tablets are:

- Strong prescription pain medicines that contains an opioid (narcotic) that is used to manage pain severe enough to require an opioid analgesic, when other pain treatments such as non-opioid pain medicines do not treat your pain well enough or you cannot tolerate them.
- Opioid pain medicines that can put you at risk for overdose and death. Even if you take your dose correctly as prescribed you are at risk for opioid addiction, abuse, and misuse that can lead to death.

Importantinformationabout hydromorphone hydrochloride:

- Get emergency help right away if you take too much hydromorphone hydrochloride tablets (overdose). When you first start taking hydromorphone hydrochloride tablets, when your dose is changed, or if you take too much (overdose), serious or life-threatening breathing problems that can lead to death may occur.
- Taking hydromorphonehydrochloride tablets with other opioid medicines, benzodiazepines, alcohol, or other central nervous system depressants (including street drugs) can cause severe drowsiness, decreased awareness, breathing problems, coma, and death.
- Never give anyone else your hydromorphone hydrochloride tablets. They could die from taking it. Store hydromorphone hydrochloride tablets away from children and in a safe place to prevent stealing or abuse. Selling or giving away hydromorphone hydrochloride tablets is against the law.

Do not take hydromorphone hydrochloride tablets if you have:

- severe asthma, trouble breathing, or other lung problems.
- a bowel blockage or have narrowing of the stomach or intestines.

Beforetaking hydromorphone hydrochloride tablets, tell your healthcare provider if you have a history of:

- head injury, seizures ● liver, kidney, thyroid problems
- problems urinating ● pancreas or gallbladder problems
- abuse of street or prescription drugs, alcohol addiction, or mental health problems.

Tell your healthcare provider if you are:

- pregnantor planning to become pregnant. Prolonged use of hydromorphone hydrochloride tablets during pregnancy can cause withdrawal symptoms in your newborn baby that could be life-threatening if not recognized and treated.
- breastfeeding. Hydromorphone hydrochloride pass into breast milk and may harm your baby.
- taking prescription or over-the-counter medicines, vitamins, or herbal supplements. Taking hydromorphone hydrochloride with certain other medicines can cause serious side effects that could lead to death.

When taking hydromorphone hydrochloride:

- Do not change your dose. Take hydromorphone hydrochloride exactly as prescribed by your healthcare provider. Use the lowest dose possible for the shortest time needed.
- Do not take more than your prescribed dose. If you miss a dose, take your next dose at your usual time.
- Call your healthcare provider if the dose you are taking does not control your pain.
- If you have been taking hydromorphone hydrochloride tablets regularly, do not stop taking hydromorphone hydrochloride tablets without talking to your healthcare provider.
- After you stop taking hydromorphone hydrochloride tablets flush any unused tablets down the toilet.

While taking hydromorphone hydrochloride DO NOT:

- Drive or operate heavy machinery, until you know how hydromorphone hydrochloride Tablets affects you. Hydromorphone hydrochloride can make you sleepy, dizzy, or lightheaded.
- Drink alcohol or use prescription or over-the-counter medicines that contain alcohol. Using products containing alcohol during treatment with hydromorphone hydrochloride tablets may cause you to overdose and die.

The possible side effects of hydromorphone hydrochloride tablets:

- constipation, nausea, sleepiness, vomiting, tiredness, headache, dizziness, abdominal pain. Call your healthcare provider if you have any of these symptoms and they are severe.

Get emergency medical help if you have:

- trouble breathing, shortness of breath, fast heartbeat, chest pain, swelling of your face, tongue, or throat, extreme drowsiness, light-headedness when changing positions, feeling faint, agitation, high body temperature, trouble walking, stiff muscles, or mental changes such as confusion.

These are not all the possible side effects of hydromorphone hydrochloride tablets. Call your doctor for medical advice about side effects. You may report side effects to FDA at 1-800-FDA-1088.

Manufactured by: Ascent Pharmaceuticals Inc, Central Islip, NY 11722, or call 1-855-221-1622

ThisMedication Guide has been approved by the U.S. Food and Drug Administration. Rev: 07/17